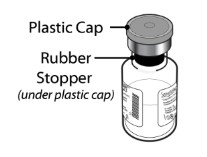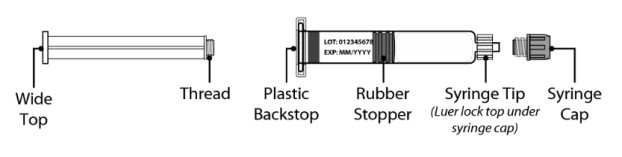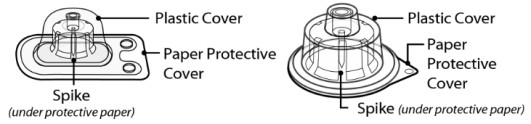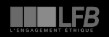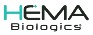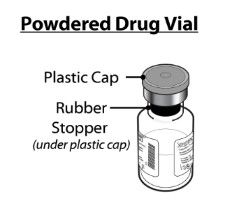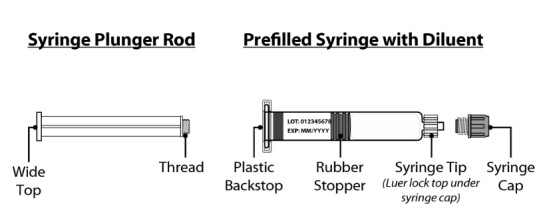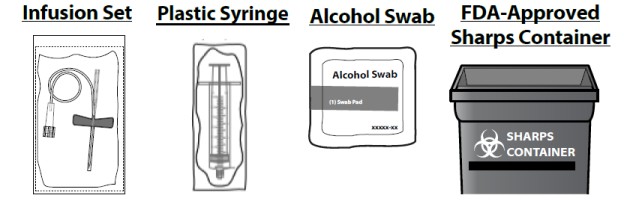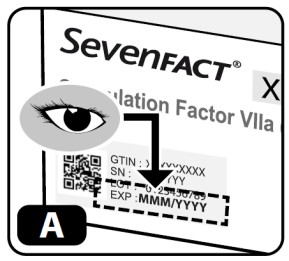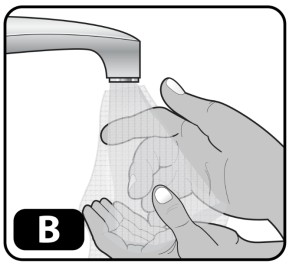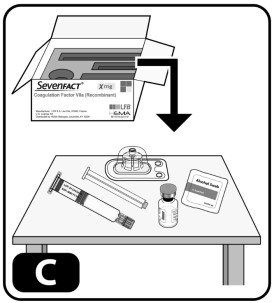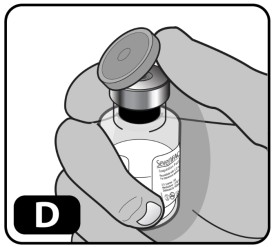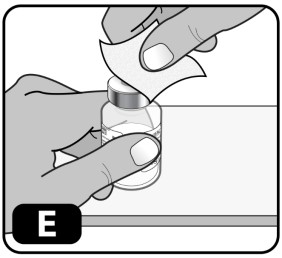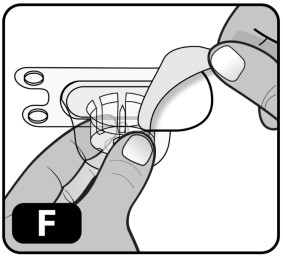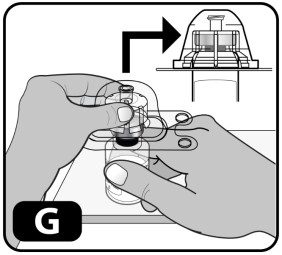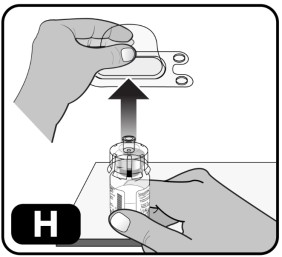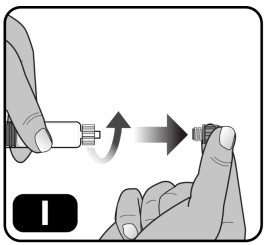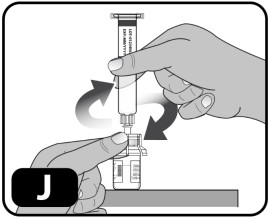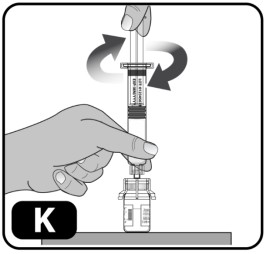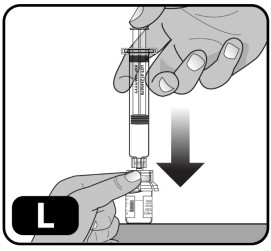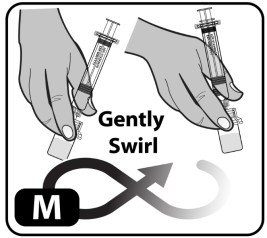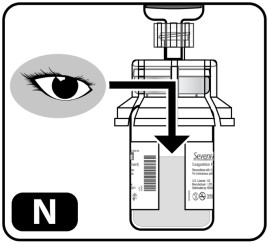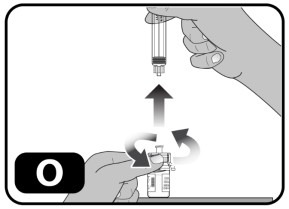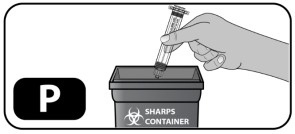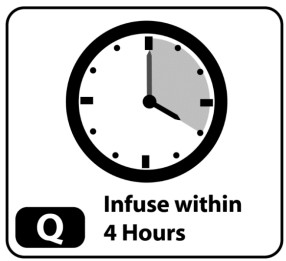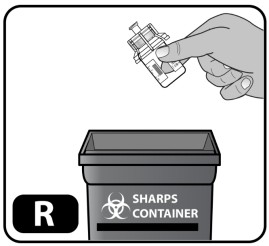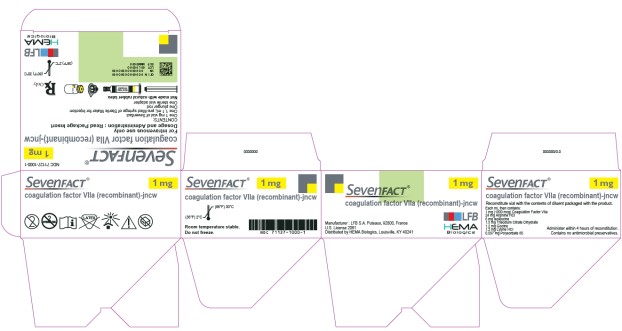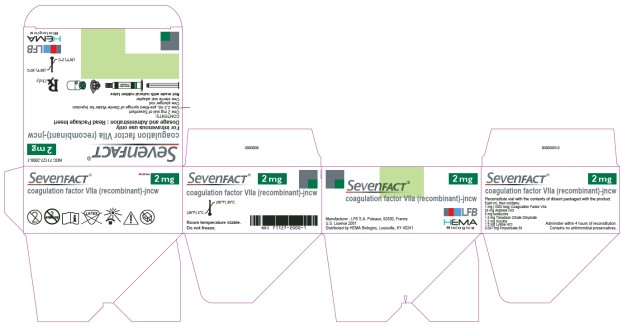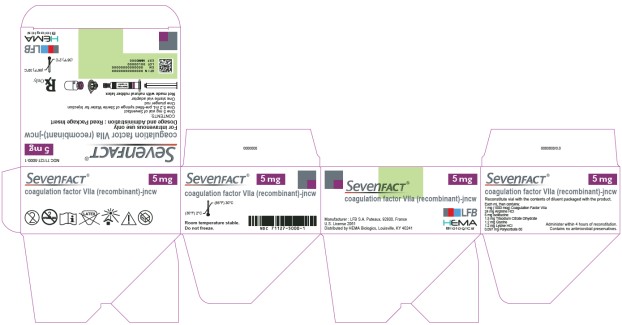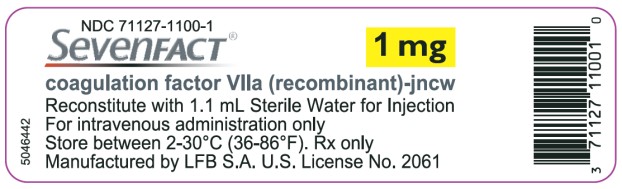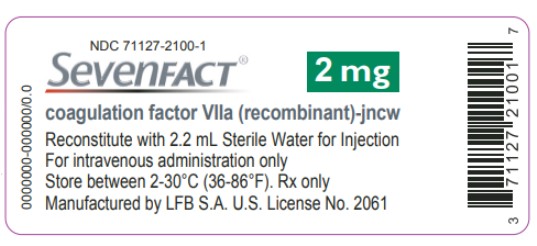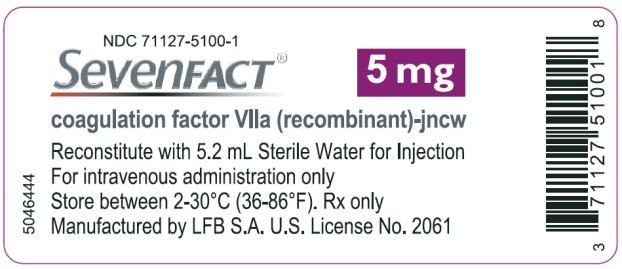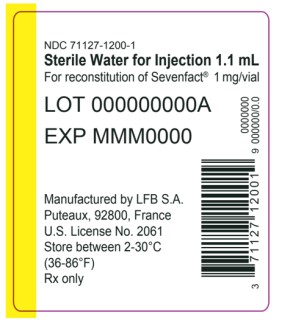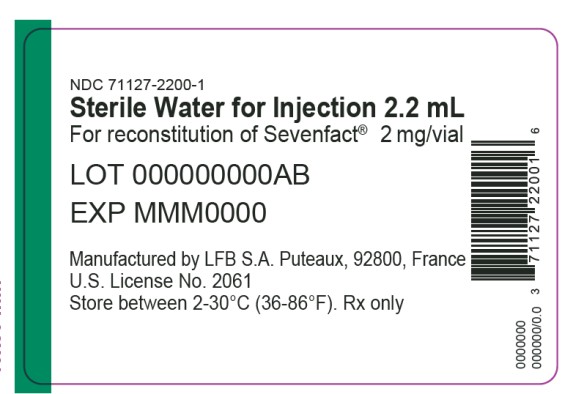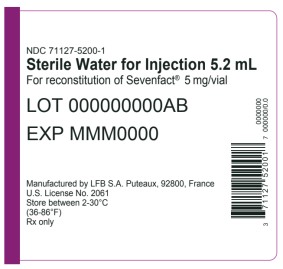 DRUG LABEL: Sevenfact
NDC: 71127-1000 | Form: KIT | Route: INTRAVENOUS
Manufacturer: Laboratoire Français du Fractionnement et des Biotechnologies Société Anonyme (LFB S.A.)
Category: prescription | Type: HUMAN PRESCRIPTION DRUG LABEL
Date: 20251119

ACTIVE INGREDIENTS: COAGULATION FACTOR VIIA RECOMBINANT HUMAN 1 mg/1 mL
INACTIVE INGREDIENTS: ARGININE HYDROCHLORIDE 24 mg/1 mL; ISOLEUCINE 6 mg/1 mL; TRISODIUM CITRATE DIHYDRATE 1.5 mg/1 mL; GLYCINE 1.2 mg/1 mL; LYSINE HYDROCHLORIDE 1.2 mg/1 mL; POLYSORBATE 80 0.097 mg/1 mL; WATER 1.1 mL/1.1 mL

HIGHLIGHTS OF PRESCRIBING INFORMATION

These highlights do not include all the information needed to use SEVENFACT® safely and effectively. See full prescribing information for SEVENFACT®.
SEVENFACT® [coagulation factor VIIa (recombinant)-jncw]
Lyophilized Powder for Solution, for Intravenous Use
Initial U.S. Approval: 2020

WARNING: THROMBOSIS

See full prescribing information for complete boxed warning.

● Serious arterial and venous thrombotic events may occur following administration of SEVENFACT® (5.1).

● Discuss the risks and explain the signs and symptoms of thrombotic and thromboembolic events to patients who will receive SEVENFACT®.

● Monitor patients for signs or symptoms of activation of the coagulation system and for thrombosis.

1 INDICATIONS AND USAGE

SEVENFACT is a coagulation factor VIIa concentrate indicated for the treatment and control of bleeding episodes occurring in adults and adolescents 12 years of age and older with hemophilia A or B with inhibitors (1).

Limitations of Use:

SEVENFACT is not indicated for treatment of congenital factor VII deficiency.

2 DOSAGE AND ADMINISTRATION

For intravenous use after reconstitution only.

Type of Bleeding | Dosing Regimen Recommendation
For Mild or Moderate bleeds | 75 mcg/kg repeated every 3 hours until hemostasis is achieved or Initial dose of 225 mcg/kg. If hemostasis is not achieved within 9 hours, additional 75 mcg/kg doses may be administered every 3 hours as needed to achieve hemostasis
For Severe bleeds | 225 mcg/kg, followed if necessary 6 hours later with 75 mcg/kg every 2 hours

Consider alternative treatments if successful control of bleeding does not occur within 24 hours of the first administration of SEVENFACT.

3 DOSAGE FORMS AND STRENGTHS

SEVENFACT is available as a lyophilized powder in single-dose vials containing 1 mg, 2 mg or 5 mg of coagulation factor VIIa (recombinant)-jncw. After reconstitution with a specified volume of Sterile Water for Injection, each mL contains 1 mg (1000 mcg) of coagulation factor VIIa (recombinant)-jncw (3).

4 CONTRAINDICATIONS

Known allergy to rabbits or rabbit proteins. Severe hypersensitivity reaction to SEVENFACT or any of its components (4).

5 WARNINGS AND PRECAUTIONS

- Patients with hemophilia A or B with inhibitors who have other risk factors for thrombosis may be at increased risk of serious arterial and venous thrombotic events (5.1).
- Hypersensitivity reactions, including anaphylaxis, are possible with SEVENFACT. Should symptoms occur, patients should discontinue SEVENFACT and seek appropriate medical intervention (5.2).

6 ADVERSE REACTIONS

The most common adverse reactions (incidence ≥1%) were headache, dizziness, infusion-site discomfort, infusion-site hematoma, infusion-related reaction, and fever (6).

To report SUSPECTED ADVERSE REACTIONS, contact HEMA Biologics at 855-718-HEMA (4362) or FDA at 1-800-FDA-1088 or https://www.fda.gov/medwatch.

7 DRUG INTERACTIONS

Clinical experience with pharmacologic use of FVIIa-containing products indicates an elevated risk of serious thrombotic events when used simultaneously with activated prothrombin complex concentrates (7).

FULL PRESCRIBING INFORMATION

WARNING: THROMBOSIS

● Serious arterial and venous thrombotic events may occur following administration of SEVENFACT®. [See Warnings and Precautions (5.1)]

● Discuss the risks and explain the signs and symptoms of thrombotic and thromboembolic events to patients who will receive SEVENFACT®.

● Monitor patients for signs or symptoms of activation of the coagulation system and for thrombosis.

1 INDICATIONS AND USAGE

SEVENFACT is indicated for the treatment and control of bleeding episodes occurring in adults and adolescents 12 years of age and older with hemophilia A or B with inhibitors.

Limitations of Use:

SEVENFACT is not indicated for the treatment of patients with congenital Factor VII deficiency.

2 DOSAGE AND ADMINISTRATION

2.1 Dose

For intravenous use after reconstitution only.

- Dose and duration of SEVENFACT depend on the location and severity of the bleeding, need for urgent hemostasis, frequency of administration, and known patient responsiveness to FVIIa-containing bypassing agents during prior bleeding events. Treatment with SEVENFACT should be initiated as soon as a bleeding event occurs.
- The dose, frequency, and duration of SEVENFACT therapy should be based on the patient’s clinical response and hemostasis evaluation.
- The use of laboratory assessment(s) of coagulation (PT/INR, aPTT, FVII:C) does not necessarily correlate with or predict the hemostatic effectiveness of SEVENFACT.
- Dose adjustment may be required if the patient has received other procoagulant therapies prior to treatment with SEVENFACT.

Based on the clinical trial program for SEVENFACT, the recommended initial dose should be adjusted based on the criteria provided in Table 1.

Table 1 Dosing for Treatment and Control of Bleeding
Type of Bleeding | Dosing Regimen Recommendation | Duration of Therapy
Mild and Moderate Joint, superficial muscle, soft tissue and mucous membranes. | 75 mcg/kg repeated every 3 hours until hemostasis is achieved or Initial dose of 225 mcg/kg. If hemostasis is not achieved within 9 hours, additional 75 mcg/kg doses may be administered every 3 hours as needed to achieve hemostasis. Consider alternative treatments if successful control of bleeding does not occur within 24 hours of the first administration of SEVENFACT. | Continue therapy to support healing and prevent recurrent hemorrhage after hemostasis to maintain the hemostatic plug. The site and severity of bleeding should determine therapy duration.
Severe Life or limb threatening hemorrhage, iliopsoas and deep muscle with neurovascular injury, retroperitoneum, intracranial, or gastrointestinal. Patients should seek immediate medical care if signs or symptoms of severe bleeding occur in the home setting. | 225 mcg/kg initially, followed if necessary 6 hours later with 75 mcg/kg every 2 hours until hemostasis is achieved. Subsequent Dosing: After achieving hemostasis, base the decision for dosing on clinical assessment and the type of bleeding. Consider the risk of thrombosis with subsequent dosing after achieving hemostatic efficacy. | Continue therapy to support healing and prevent recurrent hemorrhage. The site and severity of bleeding and the use of other procoagulant therapies should determine therapy duration.

2.2 Reconstitution

- Follow the procedures below for reconstitution of SEVENFACT.
- Calculate the amount of SEVENFACT required and select the appropriate SEVENFACT packages containing the matching pre-filled syringe of sterile Water for Injection, and the vial adapters.
- Reconstitute each vial with the pre-filled syringe provided with each vial of SEVENFACT.

Overview of SEVENFACT Package:

Figure 1 Vial with SEVENFACT Lyophilized Powder

Lyophilized Powder Drug Vial

Figure 2 Syringe Plunger Rod and Pre-filled Syringe with Water for Injection Diluent

Syringe Plunger Rod Pre-filled Syringe with Diluent

Figure 3 SEVENFACT 1 mg and 2 mg Vial Adapter and SEVENFACT 5 mg Vial Adapter

Vial Adapters* and Packaging

1 mg and 2 mg Vial Adapter 5 mg Vial Adapter

*Note: Each SEVENFACT kit will contain only one vial adapter.

The instructions below serve as a general guideline for reconstitution of SEVENFACT.

Reconstitution:

1. Based on the prescribed dose, take out the number of SEVENFACT kits (each kit containing one vial of SEVENFACT powder and one pre-filled Water for Injection diluent syringe with one vial adapter for needleless reconstitution), an infusion set (not supplied in the kit) and an alcohol swab (not supplied in the kit). Check the expiration date on the side of the box(es) for the SEVENFACT kit(s).
2. Always use aseptic technique. Wash your hands with soap and water and dry them using a clean towel or air dry.
3. Take out the contents of one kit and one alcohol swab. Place items on a clean surface.
4. Inspect all contents of the kit. Make sure each vial has a matching colored syringe.
5. Bring SEVENFACT (lyophilized powder) and the specified pre-filled syringe (diluent) to room temperature. The specified volume of diluent corresponding to the amount of SEVENFACT is as follows:
  1 mg (1000 micrograms) vial + 1.1 mL Water for Injection diluent in pre-filled syringe
  2 mg (2000 micrograms) vial + 2.2 mL Water for Injection diluent in pre-filled syringe
  5 mg (5000 micrograms) vial + 5.2 mL Water for Injection diluent in pre-filled syringe
6. Remove the plastic cap from the SEVENFACT vials to expose the central portion of the rubber stopper. Cleanse the rubber stoppers with an alcohol swab and allow to dry prior to use.
7. Peel back the protective paper from the vial adapter. Do not remove the vial adapter from the package.
8. Place the SEVENFACT vial on a flat surface. While holding the vial adapter package, place the vial adapter over the SEVENFACT vial and press down firmly on the package until the vial adapter spike breaks through the rubber stopper.
9. Lightly squeeze the plastic cover and lift up to remove it from the vial adapter. Note: the 5 mg vial adapter may not sit flat against the vial, but it is fully functional.
10. Remove the syringe cap from the pre-filled syringe by holding the syringe body with one hand to unscrew the syringe cap (turn to the left).
11. While holding the edges of the vial adapter, screw on the pre-filled syringe (turn to the right) a few turns until it starts to tighten.
12. Insert the plunger rod into the syringe, then screw a few turns (turn to the right) so that the plunger rod is attached to the gray rubber stopper in the syringe.
13. Push the plunger rod to slowly inject all the diluent into the vial. Keep the plunger rod pressed down and swirl the vial gently until the powder is dissolved.
14. The reconstituted solution is clear to slightly opaque. All powder must be mixed with no particles floating in the liquid.
15. Without withdrawing any drug back into the syringe, unscrew the syringe from the vial adapter (turn to the left) until it is completely detached.
16. Withdraw the liquid drug from the vial(s), using an infusion syringe provided by the pharmacy; the syringe should be large enough to hold the prescribed dose.
17. The reconstituted solution should be stored in the vial at room temperature, but can be stored between 36oF to 86oF (2oC to 30oC) for up to 4 hours after reconstitution. After reconstitution with the specified volume of diluent, each vial contains approximately 1 mg per mL SEVENFACT (1000 micrograms per mL).

2.3 Administration

For Intravenous Use Only.

- Visually inspect the reconstituted solution for particulate matter and discoloration prior to administration. Do not use if particulate matter or discoloration is observed.
- Do not freeze reconstituted solution or store it in a syringe.
- SEVENFACT must be infused within 4 hours after reconstitution.
- SEVENFACT should be infused over 2 minutes or less as a bolus intravenous infusion.
- Do not mix with other infusion solutions.
- Any unused solution should be discarded 4 hours after reconstitution.

3 DOSAGE FORMS AND STRENGTHS

SEVENFACT is a white to off-white lyophilized powder for reconstitution in a colorless solution for injection. It is supplied in single-dose vial sizes containing 1 mg, 2 mg or 5 mg of coagulation factor VIIa (recombinant)-jncw.

The diluent for reconstitution of SEVENFACT is supplied in single-dose prefilled glass syringes containing 1.1 mL, 2.2 mL or 5.2 mL sterile Water for Injection. It is a clear colorless solution.

After reconstitution with the appropriate volume of Water for Injection diluent, each mL of SEVENFACT contains 1 mg per mL of coagulation factor VIIa (recombinant)-jncw (1,000 micrograms per mL).

4 CONTRAINDICATIONS

SEVENFACT is contraindicated in patients with:

- known allergy to rabbits or rabbit proteins. Exposure to SEVENFACT in these patients can result in severe hypersensitivity reaction.
- severe hypersensitivity reaction to SEVENFACT or any of its components. Exposure to SEVENFACT in these patients can result in severe hypersensitivity reaction.

5 WARNINGS AND PRECAUTIONS

5.1 Thrombosis

Serious arterial and venous thrombosis can occur with coagulation factor VIIa containing products including SEVENFACT.

The following patients may have increased risk of thrombosis with use of SEVENFACT:

- History of congenital or acquired hemophilia receiving concomitant treatment with aPCC/PCC (activated or non-activated prothrombin complex) or other hemostatic agents
- History of atherosclerotic disease, coronary artery disease, cerebrovascular disease, crush injury, septicemia, or thromboembolism.
- Monitor patients who receive SEVENFACT for the development of signs and symptoms of activation of the coagulation system or thrombosis. When there is laboratory confirmation of intravascular coagulation or presence of clinical thrombosis, reduce the dose of SEVENFACT or stop treatment, depending on the patient’s condition.

5.2 Hypersensitivity and Infusion-Related Reactions

Hypersensitivity and infusion-related reactions including anaphylaxis can occur with coagulation factor VIIa containing products including SEVENFACT. Sign and symptoms may include hives, itching, rash, difficulty breathing, swelling around the mouth and throat, tightness of the chest, wheezing, dizziness or fainting, and low blood pressure. Patients with known IgE-based hypersensitivity to casein may be at higher risk of hypersensitivity reactions. In the event of hypersensitivity or infusion-related reactions, discontinue SEVENFACT and manage according to clinical practice guideline.

5.3 Neutralizing Antibodies

Neutralizing antibodies may occur with the use of SEVENFACT. If treatment with SEVENFACT does not result in adequate hemostasis, then suspect development of neutralizing antibody as the possible cause and perform testing as clinically indicated.

Neutralizing antibodies to other Factor VIIa-containing products have been observed in congenital Factor VII-deficient patients. SEVENFACT has not been studied in this patient population. [See limitation of use statement under Indications and Usage (1)].

5.4 Laboratory Tests

Laboratory coagulation parameters (PT/INR, aPTT, FVII:C) do not correlate with clinical response to SEVENFACT treatment.

6 ADVERSE REACTIONS

6.1 Clinical Trials Experience

Because clinical trials are conducted under widely varying conditions, adverse reaction rates observed in the clinical trials of a drug cannot be directly compared to rates in the clinical trials of another drug and may not reflect the rates observed in practice.

The safety database described in this section reflect exposure to SEVENFACT in two clinical studies, Study 1 and Study 2. A total of 42 patients with Hemophilia A or B with or without inhibitors received SEVENFACT: 27 patients in Study 1 at doses 75 mcg/kg and 225 mcg/kg and 15 patients in Study 2 at three escalating dose levels 25 mcg/kg, 75 mcg/kg and 225 mcg/kg [see Clinical Studies (14)].

The most common adverse reactions (incidence ≥1%) reported in clinical trials for SEVENFACT were headache, dizziness, infusion-site discomfort, infusion-site hematoma, infusion-related reaction, and fever.

Adverse reactions reported in the two clinical studies are shown in Table 2.

Table 2 Adverse Reactions Occurring in Clinical Studies
Preferred Terms | Number of Patient Adverse Reactions (% Incidence Rate) Study 2 (N=15) | Number of Adverse Reactions* Study 2 | Number of Patient Adverse Reactions (% Incidence Rate) Study 1 (N=27) | Number of Adverse Reactions* Study 1
Infusion site discomfort | - | - | 1 (4) | 4
Infusion site hematoma | - | - | 1 (4) | 2
Dizziness | 1 (7) | 2 | - | -
Headache | 1 (7) | 1 | - | -
Body temperature increase | - | - | 1 (4) | 1
Infusion related reaction** | 1 (7) | 1 | - | -

* Three patients experienced adverse reactions in Study 2 and two patients experienced adverse reactions in Study 1.

** Symptoms resolved without any intervention and did not recur with subsequent administration.

7 DRUG INTERACTIONS

Clinical experience with pharmacologic use of FVIIa-containing products indicates an elevated risk of serious thrombotic events when used simultaneously with activated prothrombin complex concentrates.

8 USE IN SPECIFIC POPULATIONS

8.1 Pregnancy

Risk Summary

There are no adequate and well-controlled studies using SEVENFACT in pregnant women to determine whether there is a drug-associated risk. Animal studies evaluating the embryo-fetal teratogenic potential of SEVENFACT have not been conducted. It is unknown whether SEVENFACT can cause fetal harm when administered to a pregnant woman or can affect fertility.

In the U.S. general population, the estimated background risks of major birth defect and miscarriage in clinically recognized pregnancies are 2-4% and 15-20%, respectively.

8.2 Lactation

Risk Summary

There is no information regarding the presence of SEVENFACT in human milk, the effect on the breastfed infant, and the effects on milk production. The developmental and health benefits of breastfeeding should be considered along with the mother’s clinical need for SEVENFACT and any potential adverse effects on the breastfed infant from SEVENFACT or from the underlying maternal condition.

8.3 Females and Males of Reproductive Potential

Risk Summary

In Study 1, male patients cautioned to avoid sexual activity without condoms received SEVENFACT for the treatment of bleeding episodes. No pregnancies from sexual partners were reported. The relative benefits of SEVENFACT should be weighed against any potential risk arising from exposure in sexually active patients.

All clinical studies of SEVENFACT were performed on males, as males are predominantly affected with the congenital form of hemophilia. No adverse effects on the mating index, fertility, or conception rate were observed following administration of SEVENFACT at dose levels up to 13-fold higher than the highest recommended human dose in healthy male rats prior to and during cohabitation with healthy untreated female rats [See Carcinogenesis, Mutagenesis, Impairment of Fertility (13.1)].

8.4 Pediatric Use

The safety and effectiveness of SEVENFACT have been established for pediatric patients ≥ 12 years of age for the treatment and control of bleeding episodes. Limited clinical data for SEVENFACT in adolescents (≥12 to <18 years) were collected in an adult and adolescent study (Study 1). A total of five patients were dosed with SEVENFACT. These five patients were treated for a total of 79 bleeding episodes (all mild or moderate) that occurred while patients were still under 18 years of age. Hemostatic efficacy in this subgroup (n=5) was comparable to efficacy observed in the overall population [See Clinical Studies (14)].

The safety and effectiveness of SEVENFACT for the treatment and control of bleeding episodes have not been established in children < 12 years of age. Effectiveness was not demonstrated in a trial of 25 pediatric patients 6 months to < 12 years of age. The safety and effectiveness of SEVENFACT in infants less than 6 months of age have not been evaluated.

8.5 Geriatric Use

Safety and effectiveness of SEVENFACT in patients >65 years of age have not been evaluated in clinical trials (Study 1 and Study 2). The presence of age-related comorbidities and the attendant risks associated with thrombotic and thromboembolic events should be considered when administering SEVENFACT to patients older than 50 years of age.

11 DESCRIPTION

SEVENFACT [coagulation factor VIIa (recombinant)-jncw] is a sterile, white to off-white lyophilized powder in a single-dose vial containing either 1 mg, 2 mg or 5 mg of coagulation factor VIIa (recombinant)-jncw as the active ingredient. SEVENFACT is to be reconstituted with Sterile Water for Injection in a pre-filled syringe supplied with the product. The reconstituted product is a clear to slightly opaque solution of coagulation factor VIIa (recombinant)-jncw at a concentration of 1 mg of protein per mL with a pH of approximately 6.0. SEVENFACT is formulated with arginine, isoleucine, citrate, glycine, lysine and polysorbate 80. It does not contain any antimicrobial preservatives nor human or bovine plasma-derived proteins.

The active ingredient in SEVENFACT, activated coagulation Factor VII, is a glycoprotein of 406 amino acids with a molecular weight of approximately 50 kilodaltons. The amino acid sequence of activated coagulation Factor VII is identical to that of human plasma-derived Factor VIIa. It is >99% pure with a nominal specific activity of 45,000 IU/mg of protein when tested against the World Health Organization international standard for human Factor VIIa activity.

SEVENFACT is produced by recombinant DNA technology using genetically engineered rabbits into which the DNA coding sequence for human Factor VII has been introduced. Human Factor VII is expressed in the rabbit mammary gland and secreted into the milk. During purification and processing, Factor VII is enzymatically converted to activated Factor VII. The manufacturing process of SEVENFACT includes specific steps to reduce impurities. SEVENFACT may contain trace amounts of rabbit proteins. The purification process also includes steps that are validated to inactivate or remove viruses, such as Xenotropic murine leukemia virus (X-MuLV), bovine viral diarrhea virus (BVDV), Pseudorabies virus (PRV), Feline Calicivirus (FCV), and Porcine Parvovirus (PPV).

12 CLINICAL PHARMACOLOGY

12.1 Mechanism of Action

The active ingredient in SEVENFACT is a recombinant analog of human Factor VIIa, a vitamin K-dependent coagulation factor. In the presence of both calcium and phospholipids, Factor VIIa in a complex with tissue factor (TF) activates Factor X to Factor Xa, directly bypassing the reactions that require Factor VIII or Factor IX. Activation of Factor X to Factor Xa initiates the common pathway of the coagulation cascade in which prothrombin is activated to thrombin, which then converts fibrinogen to fibrin to form a hemostatic plug, thereby achieving clot formation at the site of hemorrhage (hemostasis). This process may also occur in the absence of TF on the surface of activated platelets.

12.2 Pharmacodynamics

Laboratory assessment of coagulation does not necessarily correlate with or predict the hemostatic effectiveness of SEVENFACT.

SEVENFACT demonstrated a dose and concentration-dependent pharmacodynamics effect on the coagulation system, including shortening of the activated partial thromboplastin time (aPTT) and the prothrombin time (PT), and increasing the thrombin generation with platelets (TGT) and the maximum clot firmness (ROTEM-FIBTEM test).

12.3 Pharmacokinetics

Pharmacokinetic (PK) evaluation was conducted in an open-label, randomized, dose-comparison study to evaluate safety and pharmacokinetic of SEVENFACT in 28 adult patients (ages 18-75 yrs) with hemophilia A with or without inhibitors who were not actively bleeding. Patients received a single intravenous administration of either 75 mcg/kg or 225 mcg/kg dose of SEVENFACT. The PK parameters evaluated were maximum plasma concentration (Cmax) of FVIIa (ng/mL), clearance (L/h), volume of distribution (Vss (L)), area under the plasma concentration-time curve from Time 0 (dosing) to infinity (AUC0-inf) (ng*h/mL), and half-life time (t1/2 (h)), calculated from non-compartmental analysis (NCA) PK analyses using a validated activity assay.

Table 3 Pharmacokinetic Parameters of SEVENFACT (Arithmetic Mean [CV%])
PK Parameter (Arithmetic Mean [CV%]) | Cmax (ng/mL) | Clearance (L/h) | Vss (L) | AUC 0-inf (ng*h/mL) | t 1/2 (h)
75 mcg/kg (n=14) | 938 (37) | 5.1 (37) | 8.2 (37) | 1108 (447) | 2.3 (16)
225 mcg/kg (n=14) | 3211 (23) | 4.5 (20) | 7.0 (22) | 3571 (26) | 2.0 (8)

Five minutes after infusion, plasma SEVENFACT levels were 938 ng/mL and 3211 ng/mL for 75 mcg/kg and 225 mcg/kg dose groups respectively. Observed plasma concentration-time profiles show a biexponential decay from the maximal concentration to return to baseline approximately 8 hours post-administration. Exposure PK parameters Cmax and AUC0-inf suggested dose dependence over the ranges studied. The clearance of SEVENFACT was approximately 5.1 L/h and 4.5 L/h for 75 mcg/kg and 225 mcg/kg dose levels respectively. Half-life time was approximately 2 hours at both levels. Results were based on Non-Compartmental Analysis. (Table 3)

12.6 Immunogenicity

The observed incidence of anti-drug antibodies is highly dependent on the sensitivity and specificity of the assay. Differences in assay methods preclude meaningful comparisons of the incidence of anti-drug antibodies in the studies described below with the incidence of anti-drug antibodies in other studies, including those of SEVENFACT or of other Factor VIIa containing products.

In Study 1, two out of 27 patients had a positive screening assay for anti-SEVENFACT antibody at baseline, prior to exposure to SEVENFACT, and at follow-up visits. One of these two patients had a transient SEVENFACT antibody with an additional confirmatory test for anti-SEVENFACT antibody, which was confirmed as non-neutralizing.

In Study 2, five of 15 patients tested positive for anti-SEVENFACT antibody using a screening assay. The confirmatory assay was negative for all patients at all time points.

No patient developed anti-rabbit milk protein antibodies during treatment with SEVENFACT.

There was no identified clinically significant effect of anti-drug antibodies on pharmacokinetics, pharmacodynamics, safety, or effectiveness of SEVENFACT over the study duration.

13 NONCLINICAL TOXICOLOGY

13.1 Carcinogenesis, Mutagenesis, Impairment of Fertility

Studies in animals to evaluate the potential effect of SEVENFACT on carcinogenesis or mutagenesis were not conducted. Male rats intravenously infused with SEVENFACT at 0.1, 0.3, 1 and 3 mg/kg/day (up to 13-fold higher than the highest recommended human dose of 225 mcg/kg), beginning 28 days before cohabitation and during cohabitation did not display adverse effects for the mating index, fertility, or conception rate. Comparing animals administered vehicle to animals administered SEVENFACT, there were no differences in sperm motility, morphology, or concentration.

13.2 Animal Toxicology and/or Pharmacology

The no observed adverse effect level (NOAEL) in 28-day repeat-dose toxicity studies in male Sprague-Dawley rats and Cynomolgus monkeys was 1 mg/kg/day, which is 4-fold higher than the highest recommended human dose. Anti-drug antibody formation was observed by Day 29 in both animal species. The NOAEL in a 13-week repeat-dose toxicity study in male and female Cynomolgus monkeys was 1 mg/kg/day. Anti-drug antibody formation was observed in all animals by Day 28. Antibody presence was not associated with any adverse effects in either animal species.

14 CLINICAL STUDIES

The efficacy and safety of SEVENFACT for treatment of bleeding episodes was evaluated in Study 1, a global, multicenter, randomized, open-label, cross-over study (NCT02020369). The study enrolled 27 patients with hemophilia A or B with inhibitors who were treated for 468 bleeding events, of which 465 were mild or moderate and three were severe bleeding events.

The population characteristics were as follows: Mean age was 31 years (range 12 to 54 years) including five patients 12 to < 18 years of age who experienced 79 bleeding events. Patients were male, predominantly Caucasian (93%), median of 10 (range 3-50) bleeding episodes in six months prior to study enrollment. Overall, target joint(s)/bleeding site(s) were reported in 63% of patients at study entry.

Of the 468 bleeding events in diverse anatomic locations that were treated, 82% were spontaneous and the remaining (18%) were traumatic bleeding episodes; 465 were mild or moderate bleeding events and three were severe (refer to Table 5). The majority (98%) of bleeding events were treated at home, with 88% treated within one hour of recognition of bleeding.

Treatment Regimens for Mild or Moderate Bleeding Episodes

For mild to moderate bleeding episodes, patients were randomized to one of two initial dose regimens of SEVENFACT:

- 75 mcg/kg followed by subsequent doses of 75 mcg/kg every 3 hours as necessary to achieve hemostatic efficacy. A total of eight administrations were allowed in this dose regimen.
- 225 mcg/kg dose followed nine hours later with 75 mcg/kg doses every 3 hours as necessary to achieve hemostatic efficacy. A total of six administrations were allowed in this dose regimen.

Treatment with SEVENFACT was discontinued when bleeding persisted 24 hours after the first administration of SEVENFACT.

In Study 1, patients were randomized to one of two initial dosing regimens and continued on the dose regimen for three months, after which the patients were crossed over to the other dose regimen for three months.

Treatment Regimens for Severe Bleeding Episodes

Patients in the randomized study who experienced a severe bleed were administered the initial dose of 225 mcg/kg SEVENFACT at home, and were required to receive subsequent treatments at 75 mcg/kg every two hours in a hospital or hemophilia treatment center (HTC), if additional doses were considered necessary for treatment of ongoing bleeding. If response to treatment after the first or any subsequent administrations of study drug were satisfactory (i.e., efficacy assessment was rated as “good” or “excellent”), the dosing interval was changed from two hours to three hours for 1 to 2 days, after which the interval could be increased to 4 to 12 hours, depending on the severity of the bleeding episode, for as long as needed.

Bleeding Assessment

The primary endpoint of the study was successful treatment of mild or moderate bleeding episode at 12 hours after initial SEVENFACT dose administration. Success was defined by a combination of the following: patient’s response of “good” or “excellent” using a 4-point hemostatic efficacy scale (presented in Table 4), no further treatment with SEVENFACT beyond the 12-hour time point, no other hemostatic treatment needed for the bleeding episode, no administration of blood products, and no increase in pain beyond 12 hours.

Table 4 The 4-point Hemostatic Efficacy Scale Used to Assess Efficacy of Treatment
Patient and/or HCP* Evaluation | Therapeutic Response | Description
None | Lack of hemostatic efficacy | No noticeable effect of the treatment on the bleeding or worsening of patient’s condition. Continuation of treatment with the study drug was needed.
Moderate | Lack of hemostatic efficacy | Some effect of the treatment on the bleeding was noticed (e.g., pain decreased, or bleeding signs improved) but the bleeding continued and required continued treatment with the study drug.
Good | Hemostatic efficacy | Symptoms of the bleeding (e.g., swelling, tenderness, and decreased range of motion in the case of musculoskeletal hemorrhage) had largely been reduced by the treatment, but had not completely disappeared. Symptoms had improved enough to not require more infusions of the study drug.
Excellent | Hemostatic Efficacy | Full relief of pain and cessation of objective signs of the bleeding (e.g., swelling, tenderness, and decreased range of motion in the case of musculoskeletal hemorrhage). No additional infusion of study drug was required.
*Healthcare provider

The primary efficacy analysis compared hemostatic efficacy of each dosing regimen with a prespecified objective performance criterion (OPC) of 55%. This OPC was based on historical data for hemostatic efficacy of bypassing agents. The study was powered to detect a 15% improvement over OPC for each dosing regimen. Results of the primary efficacy analysis are shown in Table 5.

Of the 465 mild or moderate bleeding episodes, 17 bleeding events were not evaluable due to missing a hemostatic efficacy assessment at 12 hours.

The proportion of mild or moderate bleeding events with hemostatic efficacy at 12 hours was 82% in the 75 mcg/kg dose regimen group and was 91% in the 225 mcg/kg dose regimen group.

Hemostatic efficacy was evaluated in 79 bleeding events in the five adolescent patients: for the 75 mcg/kg dose regimen, hemostatic efficacy was 93% (95% CI; 81%- 99%) and for the 225 mcg/kg dose regimen, it was 91% (95% CI; 77%-98%), with the confidence intervals given by the Clopper-Pearson exact method.

Table 5 Efficacy of SEVENFACT at 12 Hours for Treatment and Control of Mild or Moderate Bleeding Episodes
 | 75 mcg/kg (N=25)^1 | 225 mcg/kg (N=25)^1 | Overall (N=27)^1
Number of bleeding episodes | 252 | 213 | 465
Number of bleeds with hemostatic efficacy | 197 (78.1%) | 188 (88.2%) | 385 (82.8%)
Number of failures | 44 (17.4.%) | 19 (8.9%) | 63 (13.5%)
Number of missing | 11 (4.3%) | 6 (2.8%) | 17 (3.7%)
Proportion of bleeds with hemostatic efficacy [95% CI]^2 | 82% [72%, 91%] | 91% [84%, 98%] | 86% [78%, 93%]
p-value^3 | <0.001 | <0.001
^1 N in the column header indicates number of patients who had at least 1 bleeding episode treated with a given dose of study drug.
^2 Analysis was based on data as observed. No missing value imputation was made.
^3 p-value from 1-sided normal approximation test of H0: p ≤0.55, where p is the true proportion of successfully treated mild or moderate bleeding episodes at 12 hours, with adjustment for the correlation among bleeding episodes for a given patient. The null hypothesis of hemostatic efficacy less than or equal to 55% was rejected.
Note: Stratified by actual treatment regimen at the time of the bleeding episode.
CI = confidence interval.

The median and mean (SD) numbers of administrations per mild or moderate bleeding episode were 2.0 and 2.5 (1.75) for the 75 mcg/kg dose regimen and 1.0 and 1.4 (0.96) for the 225 mcg/kg dose regimen.

The median time to attain good or excellent assessment by the patient was six hours for the 75 mcg/kg dose regimen and three hours for the 225 mcg/kg dose regimen.

There were three severe bleeding episodes, of which one was a traumatic intramuscular bleeding episode and two were spontaneous bleeding episodes in the right hip and kidney. Hemostasis was achieved at 12 hours in the three severe bleeding events. One severe bleed was treated with three 225 mcg/kg doses administered every six hours, which was a deviation from the study protocol-specified dosing. The remaining two patients were treated with 1 and 5 doses of SEVENFACT respectively.

No patient received any alternative therapy prior to 24 hours. In addition, 97.6% of bleeding episodes treated with the 75 mcg/kg dose regimen, and 99.5% of bleeding episodes treated with the 225 mcg/kg dose regimen, did not require treatment with alternative bypassing agents.

16 HOW SUPPLIED/STORAGE AND HANDLING

How Supplied

- SEVENFACT [coagulation factor VIIa (recombinant)-jncw], is supplied as a room temperature stable, white to off-white, lyophilized powder in single-dose vials, one vial per carton. The diluent for reconstitution of SEVENFACT is Water for Injection supplied as a clear colorless solution in a pre-filled syringe.
- Single 1 mg, 2 mg or 5 mg vials of SEVENFACT are available in packages as indicated in Table 6.

Table 6 SEVENFACT Presentations
Presentation | Cap Color Indication | NDC Number | Contents
1 mg per vial | Yellow | NDC 71127-1000-1 | - One 1 mg SEVENFACT single-dose vial [NDC 71127-1100-1] - One pre-filled syringe containing 1.1 mL of Sterile Water for Injection [NDC 71127-1200-1] - One 13 mm vial adapter with 5 micron filter
2 mg per vial | Green | NDC 71127-2000-1 | - One 2 mg SEVENFACT single-dose vial [NDC 71127-2100-1] - One pre-filled syringe containing 2.2 mL of Sterile Water for Injection [NDC 71127-2200-1] - One 13 mm vial adapter with 5 micron filter
5 mg per vial | Purple | NDC 71127-5000-1 | - One 5 mg SEVENFACT single-dose vial [NDC 71127-5100-1] - One pre-filled syringe containing 5.2 mL of Sterile Water for Injection [NDC 71127-5200-1] - One 20 mm vial adapter with 5 micron filter

- The SEVENFACT vials are made of glass, closed with a bromobutyl rubber stopper (not made with natural rubber latex), and sealed with an aluminum cap.
- The pre-filled diluent syringes are made of glass, with a siliconized bromobutyl rubber plunger (not made with natural rubber latex).

Storage and Handling

- Prior to reconstitution, the SEVENFACT kit should be stored at room temperature but can be stored between 36°F to 86°F (2°C to 30°C), protected from light in the product package. Do not freeze.
- After reconstitution, SEVENFACT should be stored at room temperature but can be stored between 36°F to 86°F (2°C to 30°C), for up to 4 hours. Do not freeze or store in syringes.

17 PATIENT COUNSELING INFORMATION

Advise patients:

- to read the FDA-approved patient labeling (Patient Product Information and Instructions for Use).
- about the early signs of hypersensitivity reactions and to seek medical help if the following occur:
  - Hives, itching, rash, difficulty breathing, swelling around the mouth and throat, tightness of the chest, wheezing, dizziness or fainting, low blood pressure, or other symptoms of anaphylaxis.
- about the signs of thrombosis and to seek medical help if the following occur:
  - New-onset swelling and pain in the limbs or abdomen, new-onset chest pain, shortness of breath, loss of sensation or motor power, or altered consciousness or speech.

Revised: November 13, 2025
U.S. License Number: 2061
“SEVENFACT” is a registered trademark of LFB S.A.
PATENT Information: https://hemabiodup.wpengine.com/patents/

For Information Contact:
Call: 855.718.HEMA (4362)
Email: medinfo@hemabio.com

Manufactured by:
Laboratoire Français du Fractionnement et des Biotechnologies S.A. (LFB S.A.)
Puteaux, 92800
France

U.S. License Number: 2061

Distributed by:
HEMA Biologics
Louisville, KY 40241

U.S. License Number: 2061

Patient Product Information

SEVENFACT® (SEV-en-fact)
coagulation factor VIIa (recombinant)-jncw
For Intravenous Injection After Reconstitution Only

PLEASE READ PATIENT PRODUCT INFORMATION AND THE INSTRUCTIONS FOR USE THAT COME WITH SEVENFACT BEFORE YOU START TAKING THIS MEDICINE AND EACH TIME YOU GET A REFILL. THERE MAY BE NEW INFORMATION.

This Patient Product Information does not take the place of talking with your healthcare provider about your medical condition and treatment. If you have questions about SEVENFACT after reading this information, ask your healthcare provider.

What is the most important information I should know about SEVENFACT?

The most serious possible side effect of SEVENFACT is abnormal blood clotting involving blockage of blood vessels, which include stroke, blockage of the main blood vessel to the lung, and deep vein blood clots.

You should know the signs of abnormal clotting (thrombosis) described below and seek medical help immediately if they occur.

New onset of swelling and pain in the limbs or abdomen, new onset of chest pain, shortness of breath, loss of sensation or motor power, and altered consciousness or speech can all be signs of clot formation in places other than your site of bleeding. Seek immediate medical attention if you experience one or more of these symptoms.

SEVENFACT should be used as prescribed and directed by your healthcare provider.

What is SEVENFACT?

SEVENFACT is a recombinant human Factor VIIa protein for injection. SEVENFACT can allow adolescents and adults with Hemophilia A or B with inhibitors to create clotting at the site of bleeding without needing Coagulation Factor VIII or IX replacement.

SEVENFACT, coagulation factor VIIa (recombinant)-jncw, is indicated for the treatment and control of bleeding episodes occurring in adults and adolescents 12 years of age and older with Hemophilia A or B with inhibitors.

Injecting medications requires special training. Do not attempt to self-infuse unless you have been taught how by your health care provider or hemophilia treatment center. Once trained, you will need additional infusion materials along with your SEVENFACT so that you can successfully treat your bleeding episodes at home. Be sure to collect all necessary infusion materials before starting the reconstitution process.

SEVENFACT comes in a sterile dry powdered dosage form that must be reconstituted with sterile Water for Injection.

It is not known if SEVENFACT is safe and effective in children under 12 years of age.

Who should not USE SEVENFACT?

You should not use SEVENFACT if you:

- Are allergic to rabbits.
- Have known allergies to SEVENFACT or any of its components.

Tell your doctor prior to infusing SEVENFACT if you have begun treatment of a bleeding episode with another bypassing agent such as activated prothrombin complex concentrate (FEIBA®).

What should I tell my healthcare provider before I use SEVENFACT?

Tell your healthcare provider if you:

- Are pregnant, planning to become pregnant or nursing, as SEVENFACT has not been studied in patients with Hemophilia A or B with inhibitors who are pregnant or nursing.
- Had prior blood clots, heart disease, heart failure, abnormal heart rhythms, prior pulmonary clots or heart surgery.
- Have or have had any other medical conditions.

You and your doctor can then decide whether SEVENFACT is the right treatment for you, as well as the proper timing and doses you will need for SEVENFACT to control your bleeding episodes at home.

How should I use SEVENFACT?

Treatment with SEVENFACT should be started by a healthcare provider who is experienced in the care of patients with Hemophilia A or B with inhibitors.

SEVENFACT is given as an injection into your vein.

You may infuse SEVENFACT at a hemophilia treatment center, at your healthcare provider’s office, or in your home. You should be trained on how to infuse by your healthcare provider or hemophilia treatment center. Many people with inhibitors learn to infuse by themselves or with the help of a family member.

Treating at first sign of a bleed is important for bleed management. Your healthcare provider will tell you how much SEVENFACT to use based on your weight and when to administer SEVENFACT.

To administer SEVENFACT:

- Collect all materials needed for your prescribed dose
- Follow the Instructions For Use guide to reconstitute the prescribed number of SEVENFACT vials
- Infuse following your healthcare provider’s instructions, using infusion materials from your pharmacy

Contact your healthcare provider if you:

- Miss a dose, or
- Administer more than your prescribed dose, or
- Think your bleed is not controlled within the expected time frame discussed with your healthcare provider.

What should I avoid while using SEVENFACT?

- Avoid activity that can create more bleeding once you have completed your SEVENFACT infusion
- Avoid mixing SEVENFACT with other medications
- Avoid infusing SEVENFACT and other factor-containing therapies [such as activated prothrombin complex concentrate (aPCC) or other recombinant Factor VIIa products] at the same time. This increases your risk of having a disabling blood clot.

What are the possible side effects of SEVENFACT?

The most common adverse reactions reported in clinical trials for SEVENFACT were headache, dizziness, infusion-site discomfort, infusion-site hematoma, infusion-related reaction and fever.

A serious allergic reaction to SEVENFACT may occur. If you experience the severe symptoms of an allergic reaction after infusing SEVENFACT, seek immediate medical attention. Severe symptoms occur when your immune system reacts very strongly to foreign proteins or drugs.

- Hives, itching, rash, difficulty breathing with cough or wheezing, swelling around the mouth and throat, tightness of the chest, dizziness or fainting, and low blood pressure are all symptoms of a severe allergic reaction (anaphylaxis). Call 911 should you experience one or more of these symptoms.

These are not all the possible side effects of SEVENFACT. For more information, ask your healthcare provider or pharmacist.

Call your healthcare provider for medical advice about side effects. You may report side effects to FDA at 1-800-FDA-1088.

How should I store SEVENFACT?

- SEVENFACT should be stored in its product packaging to protect from light.
- Prior to reconstitution, the SEVENFACT kit should be stored at room temperature but can be stored between 36°F to 86°F (2°C to 30°C).
- After reconstitution, SEVENFACT should be stored at room temperature but can be stored between 36°F to 86°F (2°C to 30°C), for up to 4 hours.
- SEVENFACT should not be frozen.

General information about the safe and effective use of SEVENFACT

SEVENFACT is sometimes prescribed for purposes other than those listed here.

This leaflet summarizes the most important information about SEVENFACT.

Do not use SEVENFACT for a condition for which it was not prescribed. Do not give SEVENFACT to other people even if they have the same symptoms you have. It may harm them.

You can ask your pharmacist or healthcare provider for information about SEVENFACT that is written for health professionals.

For more information, go to www.SEVENFACT.com or call 855.718.HEMA (4362).

What are the ingredients in SEVENFACT?

Active ingredient: coagulation factor VIIa (recombinant)-jncw

Inactive ingredients: arginine hydrocholoride, glycine, isoleucine, lysine hydrochloride, polysorbate 80, trisodium citrate dihydrate, hydrochloric acid, nitrogen and water for injection.

For Information Contact:
HEMA Biologics, LLC
4441 Springdale Road
Louisville, Kentucky 40241-1086

Manufactured by:
Laboratoire Francais du Fractionnement et des Biotechnologies S.A. (LFB S.A.)
Puteaux, 92800
France

Distributed by:
HEMA Biologics
Louisville, KY 40241

U.S. License No. 2061

All trademarks are the property of their respective owners.

“SEVENFACT” is a registered trademark of LFB S.A.

PATENT Information: https://hemabiodup.wpengine.com/patents/

Revised: November 13, 2025

INSTRUCTIONS FOR USE:

READ BEFORE YOU START USING SEVENFACT®

Your healthcare provider should show you and/or your caregiver how to reconstitute and administer SEVENFACT® the first time it is used. Use aseptic techniques.

Your SEVENFACT® kit contains:

Vial Adapters* and Packaging

1 mg and 2 mg Vial Adapter 5 mg Vial Adapter

*Note: Each SEVENFACT kit will contain only one vial adapter.

You will also need:

1 Collect Supplies and Prepare Vial

- Take out the number of SEVENFACT® kits you need to fulfill your prescribed dose, an infusion set (not supplied) and an alcohol swab (not supplied).
  Do not use the kit if the tamper seal has been broken or you suspect the kit is contaminated. Use a new kit instead.

- Check the expiration date on the side of the kit (Figure A).
  Do not use if expired.

- Clean a flat surface before starting the steps for reconstituting SEVENFACT®.
- Wash your hands with soap and water and dry using a clean towel or air dry (Figure B).
- Take out the contents of one kit and one alcohol swab. Place items on the clean surface (Figure C).
- Inspect all contents of the kit. Make sure each vial has a matching colored syringe.
  Do not use the contents if they have been dropped or if they are damaged. Use a new kit instead.
- If not already at room temperature, bring the vial and the pre-filled syringe to room temperature. You can do this by holding them in your hands until they feel as warm as your hands.
- Remove the plastic cap from the vial (Figure D).
  If the plastic cap is loose or missing, do not use the vial.
- Wipe the rubber stopper with an alcohol swab (Figure E) and allow it to air dry for a few seconds to ensure that it is as germ free as possible.
- After cleaning with the swab, do not touch the rubber stopper with your fingers and do not allow it to touch any other object until you attach the vial adapter, as this can transfer germs.

2 Attach Vial Adapter

- Peel off the paper protective cover from the vial adapter package (Figure F).
- Hold the vial on the clean flat surface with one hand, using your other hand to hold the plastic cover (with the vial adapter inside) directly over the drug vial. The spike of the adapter should line up with the middle of the gray rubber stopper.
- Firmly press down so the vial adapter spike breaks through the rubber stopper (you may hear/see it "snap" into place) (Figure G).
- Lightly squeeze the plastic cover and lift up to remove it from the vial adapter (Figure H).
  Do not touch the top of the vial adapter once the plastic cover is removed to avoid transferring germs from your fingers.
  NOTE: The 5 mg vial adapter may not sit flat against the vial, but it is fully functional.

3 Attach Pre-filled Syringe and Install the Plunger Rod

- Remove the syringe cap from the pre-filled syringe by holding the syringe body with one hand and using the other hand to unscrew the syringe cap (turn to the left) (Figure I).
  Do not touch the syringe tip under the syringe cap to avoid transferring germs from your fingers.
  Do not use the pre-filled syringe if the syringe cap is loose or missing.
- While holding the edges of the vial adapter, screw on the pre-filled syringe (turn to the right) a few turns until it starts to tighten (Figure J).
  Be careful not to overtighten as you will need to remove the syringe later.
- Hold the plunger rod by the wide top end in one hand and the syringe body using your other hand.
- Insert the plunger rod into the syringe, then screw a few turns (turn to the right) so that the plunger rod is attached to the gray rubber stopper in the syringe (Figure K).

4 Mix Drug in Vial

- Very slowly push down on the plunger rod to the bottom of the syringe, to transfer all of the liquid from the syringe into the drug vial (Figure L).
  Do not push too quickly as it can result in excess foam and air in the vial.
- Swirl the vial gently or roll between hands until all powder is dissolved (Figure M).
  Do not shake the vial as this creates foam and air.
- Check the mixed solution (Figure N). It should be clear to slightly opaque. All powder should be dissolved with no particles floating in the liquid.
  Do not use the drug if liquid has particles or is cloudy after mixing. Start over with a new kit.

5 Remove Empty Syringe from Vial Adapter

- Without withdrawing any drug back into the syringe, unscrew the syringe from the vial adapter (turn to the left) until it is completely detached (Figure O).
- Throw out empty syringe into an FDA-approved sharps container (Figure P).
  Do not remove the vial adapter.
  Do not touch the luer lock top of the vial adapter. If you touch this top, germs from your fingers can be transferred.

6 Mix Additional Vial(s) and Infuse Dose

- If your dose requires more than one vial, repeat the above steps with additional kits until you have reached your required dose.
- Withdraw the liquid drug from the vial(s), using a syringe provided by your pharmacy that is large enough to hold your prescribed dose.
- SEVENFACT® must be infused within 4 hours of reconstitution (Figure Q).
  Do not use if more than 4 hours have passed since reconstitution.

- SEVENFACT® can be infused in 2 minutes or less as an intravenous infusion per the instructions of your healthcare provider.

7 Throw Out Empty Drug Vial(s)

- After reconstitution and infusion, safely dispose of the vial with vial adapter attached, the infusion syringe, and any other waste materials into an FDA-approved sharps container (Figure R).
  Do not throw out with the ordinary household trash.
  Do not disassemble the vial and vial adapter before disposal.
  Do not reuse any components of the kit.
- If you do not have an FDA-approved sharps container, you may use a container with the following:
  - Made of heavy duty plastic,
  - Can be closed, puncture resistant and prevents sharps from coming out,
  - Upright and stable,
  - Leak resistant,
  - Properly labeled as hazardous

Follow local or state guidelines for proper disposal of sharps container. For more information about safe sharps disposal visit FDA’s website: http://www.fda.gov/safesharpsdisposal

Storage

SEVENFACT® is supplied in a kit that should be stored at room temperature, but can be stored between 36°F to 86°F (2°C-30°C).

Do not open the kit contents until you are ready to use them.

Do not freeze or store in syringes reconstituted SEVENFACT® solution.

Avoid exposure of the reconstituted SEVENFACT® solution to direct light.

Important Information

SEVENFACT® is for intravenous infusion only. Do not administer through any other route (subcutaneous or intramuscular).

Contact your healthcare provider or local hemophilia treatment center if you experience problems.

For Questions or Complaints:

Call: 855.718.HEMA (4362)

https://hemabio.com/

or please contact your HEMA Biologics representative for assistance.

This Instructions for Use has been approved by the U.S. Food and Drug Administration.

Manufactured by LFB S.A. Puteaux, 92800, France

Distributed by HEMA Biologics, Louisville, KY 40241

Revised: November 13, 2025

PRINCIPAL DISPLAY PANEL

NDC 71127-1000-1

SEVENFACT® 1 mg
coagulation factor VIIa (recombinant)-jncw

For intravenous use only

Dosage and Administration: Read Package Insert

CONTENTS:
One 1 mg vial of Sevenfact
One 1.1 mL pre-filled syringe of Sterile Water for Injection
One plunger rod
One sterile vial adapter

Not made with natural rubber latex

Rx only

LFB

HEMA Biologics

PRINCIPAL DISPLAY PANEL

NDC 71127-2000-1

SEVENFACT® 2 mg
coagulation factor VIIa (recombinant)-jncw

For intravenous use only

Dosage and Administration: Read Package Insert

CONTENTS:
One 2 mg vial of Sevenfact
One 2.2 mL pre-filled syringe of Sterile Water for Injection
One plunger rod
One sterile vial adapter
Not made with natural rubber latex

Rx only

LFB

HEMA Biologics

PRINCIPAL DISPLAY PANEL

NDC 71127-5000-1

SEVENFACT® 5 mg
coagulation factor VIIa (recombinant)-jncw

For intravenous use only

Dosage and Administration: Read Package Insert

CONTENTS:
One 5 mg vial of Sevenfact
One 5.2 mL pre-filled syringe of Sterile Water for Injection
One plunger rod
One sterile vial adapter
Not made with natural rubber latex

Rx only

LFB

HEMA Biologics

PRINCIPAL DISPLAY PANEL

NDC 71127-1100-1
SEVENFACT® 1 mg
coagulation factor VIIa (recombinant)-jncw
Reconstitute with 1.1 mL Sterile Water for Injection
For intravenous administration only
Store between 2-30°C (36-86°F). Rx only
Manufactured by LFB S.A. U.S. License No. 2061

PRINCIPAL DISPLAY PANEL

NDC 71127-2100-1
SEVENFACT® 2 mg
coagulation factor VIIa (recombinant)-jncw
Reconstitute with 2.2 mL Sterile Water for Injection
For intravenous administration only
Store between 2-30°C (36-86°F). Rx only
Manufactured by LFB S.A. U.S. License No. 2061

PRINCIPAL DISPLAY PANEL

NDC 71127-5100-1
SEVENFACT® 5 mg
coagulation factor VIIa (recombinant)-jncw
Reconstitute with 5.2 mL Sterile Water for Injection
For intravenous administration only
Store between 2-30°C (36-86°F). Rx only
Manufactured by LFB S.A. U.S. License No. 2061

PRINCIPAL DISPLAY PANEL

NDC 71127-1200-1
Sterile Water for Injection 1.1 mL
For reconstitution of Sevenfact® 1 mg/vial

LOT 000000000A

EXP MMM0000

Manufactured by LFB S.A.
Puteaux, 92800, France
U.S. License No. 2061
Store between 2-30°C
(36-86°F)
Rx only

PRINCIPAL DISPLAY PANEL

NDC 71127-2200-1
Sterile Water for Injection 2.2 mL
For reconstitution of Sevenfact® 2 mg/vial

LOT 000000000AB

EXP MMM0000

Manufactured by LFB S.A. Puteaux, 92800, France
U.S. License No. 2061
Store between 2-30°C(36-86°F). Rx only

PRINCIPAL DISPLAY PANEL

NDC 71127-5200-1
Sterile Water for Injection 5.2 mL
For reconstitution of Sevenfact® 5 mg/vial

LOT 000000000AB

EXP MMM0000

Manufactured by LFB S.A. Puteaux, 92800, France
U.S. License No. 2061
Store between 2-30°C
(36-86°F)
Rx only